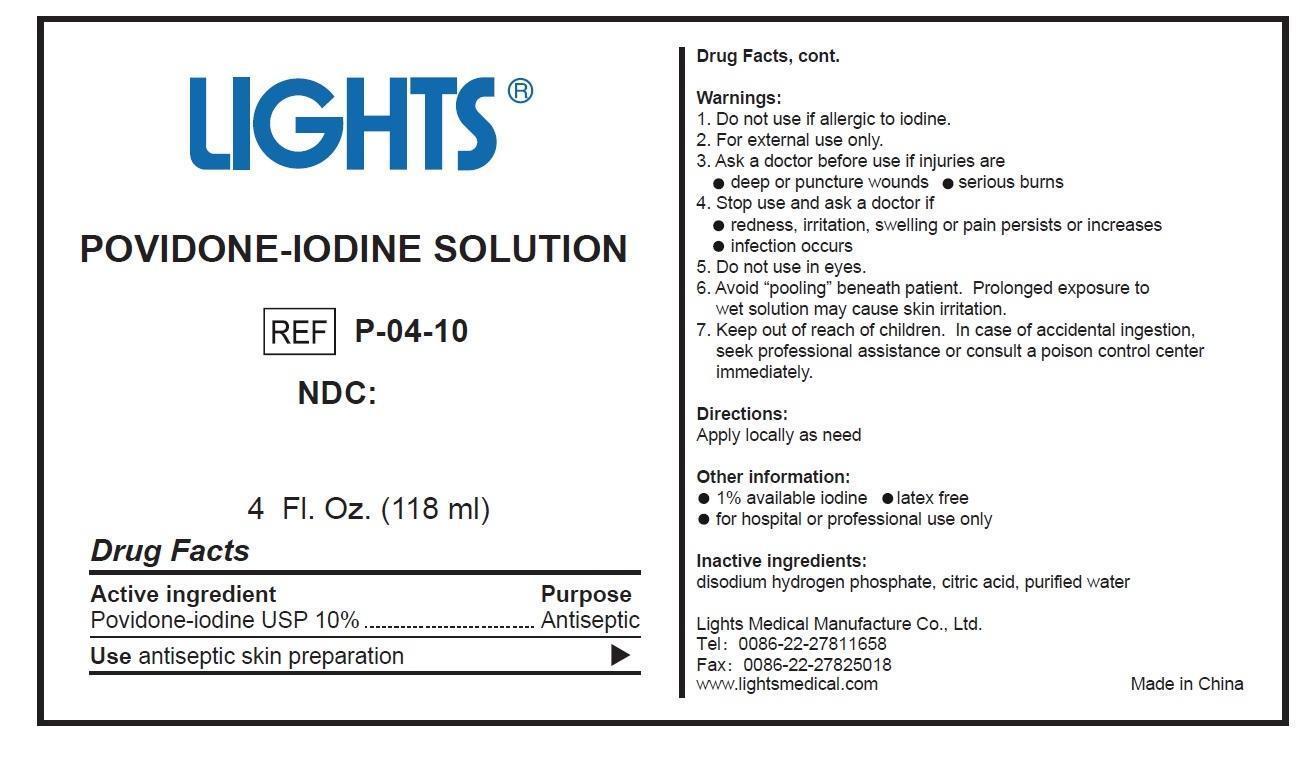 DRUG LABEL: Lights Povidone Iodine Solution
NDC: 61333-201 | Form: SOLUTION
Manufacturer: Lights Medical Manufacture Co., Ltd.
Category: otc | Type: HUMAN OTC DRUG LABEL
Date: 20260121

ACTIVE INGREDIENTS: POVIDONE-IODINE 1.18 g/118 mL
INACTIVE INGREDIENTS: WATER; CITRIC ACID MONOHYDRATE; SODIUM PHOSPHATE, DIBASIC

61333-201

Active Ingredient: Povidone-Iodine USP (10%)

Purpose: Antiseptic

INDICATIONS AND USAGE

Use: Antiseptic skin preparation

Warnings:

Do not use if allergic to iodine

For external use only

Do not use in eyes

Avoid "pooling" beneath patients. Prolonged exposure to wet solution may cause skin irritation

Keep out of reach of children. In case of accidental ingestion, seek professional assistance or consult a poison control center immediately

Ask a doctor before use if injuries are

- deep or puncture wounds
- serious burns

Stop use and ask a doctor if

- redness, irritation, swelling, or pain persists or increases
- infection occurs

DOSAGE AND ADMINISTRATION

Apply locally as need

Other information

- 1% available iodine
- latex free
- for hospital or professional use only

Inactive Ingredient

Disodium hydrogen phosphate, citric acid, water